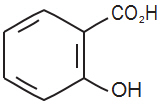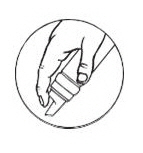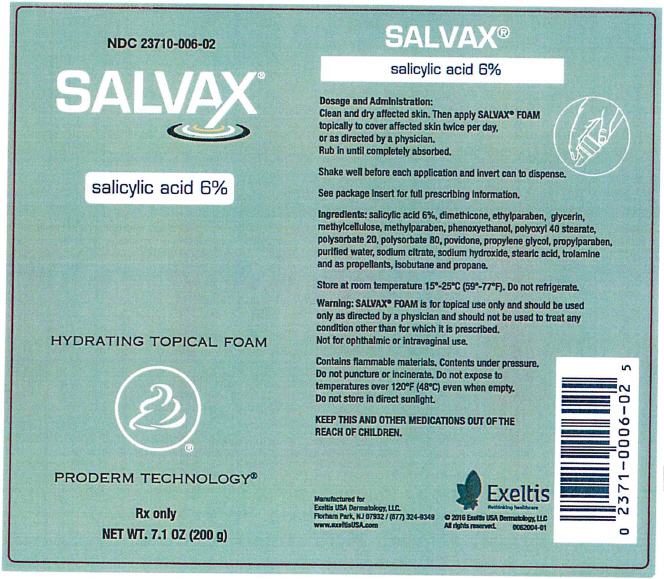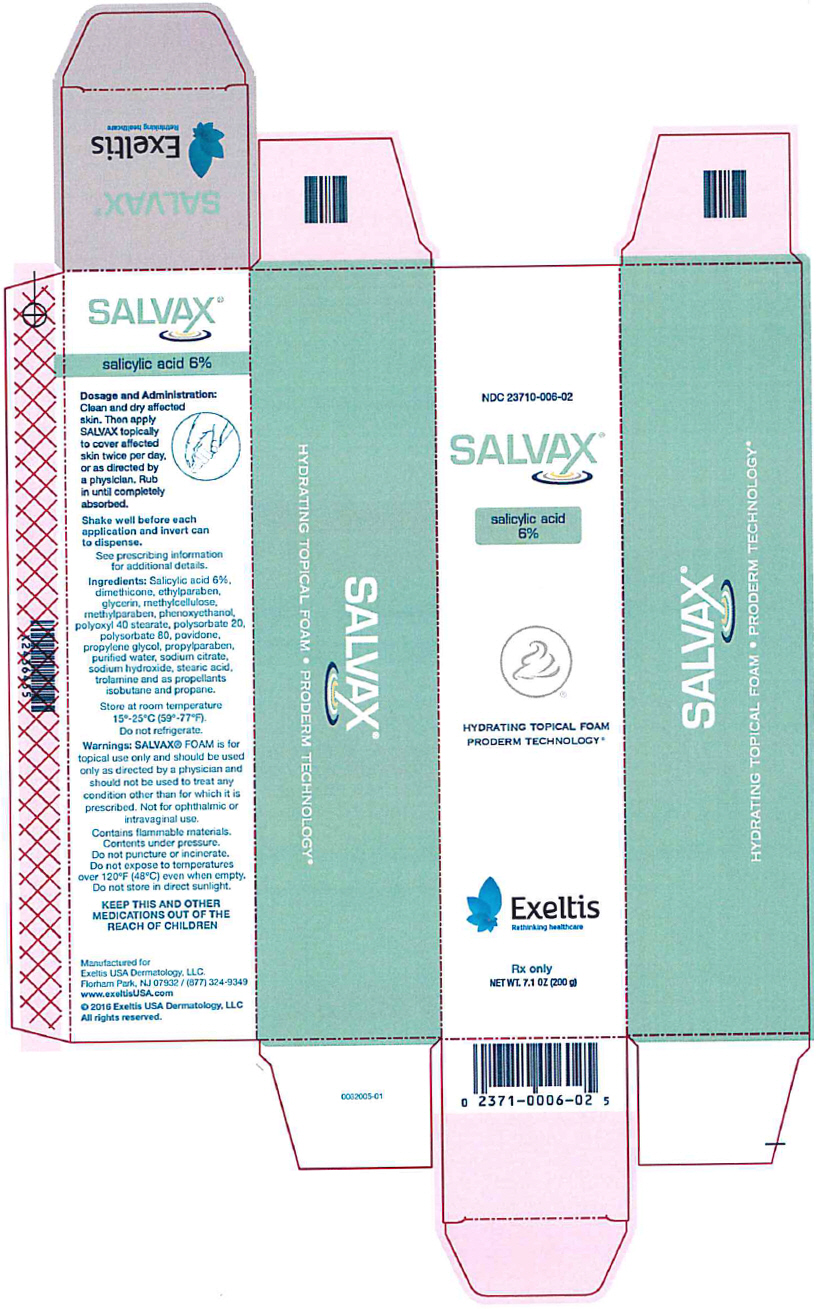 DRUG LABEL: Salvax
NDC: 23710-006 | Form: AEROSOL, FOAM
Manufacturer: Exeltis USA Dermatology, LLC
Category: prescription | Type: HUMAN PRESCRIPTION DRUG LABEL
Date: 20220101

ACTIVE INGREDIENTS: SALICYLIC ACID 3.88 g/70 g
INACTIVE INGREDIENTS: WATER; PROPYLENE GLYCOL; DIMETHICONE; CARBOXYMETHYLCELLULOSE; POLYOXYL 40 STEARATE; POLYSORBATE 20; POLYSORBATE 80; POVIDONE K30; SODIUM CITRATE, UNSPECIFIED FORM; SODIUM HYDROXIDE; STEARIC ACID; TROLAMINE; GLYCERIN; ETHYLPARABEN; PROPYLPARABEN; PHENOXYETHANOL; METHYLPARABEN; BUTANE

SALVAX®

salicylic acid, 6%

For Topical Dermatological Use Only

Hydrating Topical Foam

(salicylic acid 6% in a water and lipid based foam)

Rx Only

DESCRIPTION

SALVAX is applied topically and used in the removal of excessive keratin in hyperkeratotic skin disorders. Each gram of SALVAX contains salicylic acid 6% as the active ingredient, and the following inactive ingredients: dimethicone, ethylparaben, glycerin, methylcellulose, methylparaben, phenoxyethanol, polyoxyl 40 stearate, polysorbate 20, polysorbate 80, povidone, propylene glycol, propylparaben, purified water, sodium citrate, sodium hydroxide, stearic acid, and trolamine and as propellants isobutane and propane.

CHEMICAL STRUCTURE

Salicylic acid is the 2-hydroxy derivative of benzoic acid having the following chemical structure:

CLINICAL PHARMACOLOGY

Salicylic acid has been shown to produce desquamation of the horny layer of skin while not affecting qualitative or quantitative changes in structure of the viable epidermis. The mechanism of action has been attributed to dissolution of intercellular cement substance. In a study of the percutaneous absorption of salicylic acid from SALVAX in four patients with extensive active psoriasis, Taylor and Halprin showed that peak serum salicylate levels never exceeded 5 mg/100 ml even though more than 60% of the applied salicylic acid was absorbed. Systemic toxic reactions are usually associated with much higher serum levels (30 to 40 mg/100 ml). Peak serum levels occurred within 5 hours of the topical application under occlusion. The sites were occluded for 10 hours over the entire body surface below the neck. Since salicylates are distributed in the extracellular space, patients with a contracted extracellular space due to dehydration or diuretics have higher salicylate levels than those with a normal extracellular space. (See PRECAUTIONS).

The major metabolites identified in the urine after topical administration are salicyluric acid (52%), salicylate glucuronides (42%), and free salicylic acid (6%). The urinary metabolites after percutaneous absorption differ from those after oral salicylate administration; those derived from percutaneous absorption contain more glucuronides and less salicyluric and salicylic acid. Almost 95% of a single dose of salicylate is excreted within 24 hours of its entrance into the extracellular space.

Fifty to eighty percent of salicylate is protein bound to albumin. Salicylates compete with the binding of several drugs and can modify the action of these drugs. By similar competitive mechanisms other drugs can influence the serum levels of salicylate. (See PRECAUTIONS).

PHARMACOKINETICS

The mechanism of action of topically applied salicylic acid has been attributed to the dissolution of intercellular cement substance.

INDICATIONS AND USAGE

For dermatologic Use

SALVAX is a topical aid in the removal of excessive keratin in hyperkeratotic skin disorders, including verrucae and the various ichthyoses, keratosis palmaris and plantaris, keratosis pilaris, pityriasis rubra pilaris, and psoriasis.

For Podiatric Use

SALVAX is a topical aid in the removal of excessive keratin on dorsal and plantar hyperkeratotic lesions.

CONTRAINDICATIONS

SALVAX should not be used in any patient known to be sensitive to salicylic acid or any other listed ingredients.

WARNINGS

SALVAX is for external use only. It is not for ophthalmic, oral, anal or intravaginal use. Contact with eyes, lips, broken or inflamed skin, and all mucous membranes should be avoided. SALVAX should not be used by persons who have a known hypersensitivity to salicylic acid or any of the other listed ingredients.

Prolonged use over large areas, especially in children and those patients with significant renal or hepatic impairment could result in salicylism. Concomitant use of other drugs which may contribute to elevated serum salicylate levels should be avoided where the potential for toxicity is present. In children under 12 years of age and those patients with renal or hepatic impairment, the area to be treated should be limited and the patient monitored closely for signs of salicylate toxicity: nausea, vomiting, dizziness, loss of hearing, tinnitus, lethargy, hyperpnoea, diarrhea, psychic disturbances. In the event of salicylic acid toxicity, the use of SALVAX should be discontinued. Fluids should be administered to promote urinary excretion. Treatment with sodium bicarbonate (oral or intravenous) should be instituted as appropriate.

Considering the potential risk of developing Reye's syndrome, salicylate products should not be administered to children or teenagers with varicella or influenza, unless directed by a physician.

PRECAUTIONS

SALVAX should be used only as directed by a physician and should not be used to treat any condition other than that for which it is prescribed. SALVAX should not be used on any skin area where inflammation or exudation is present as increased absorption may occur. If redness or irritation occurs, discontinue use and consult with prescribing physician.

Drug Interactions

(The following interactions are from a published review and include reports concerning both oral and topical salicylate administration. The relationship of these interactions to the use of SALVAX is not known.)

1. Due to the competition of salicylate with other drugs for binding to serum albumin the following drug interactions may occur:
  Drug | Description of Interaction
  Tolbutamide; Sulfonylureas | Hypoglycemia potentiated
  Methotrexate | Decreases tubular reabsorption; clinical toxicity from methotrexate can result
  Oral Anticoagulants | Increased bleeding
2. Drugs changing salicylate levels by altering renal tubular reabsorption:
  Drug | Description
  Corticosteroids | Decreases plasma salicylate level; tapering doses of steroids may promote salicylism
  Ammonium Sulfate | Increases plasma salicylate level
3. Drugs with complicated interactions with salicylates:
  Drug | Description
  Heparin | Salicylate decreases platelet adhesiveness and interferes with hemostasis in heparin-treated patients
  Pyrazinamide | Inhibits pyrazinamide-induced hyperuricemia
  Uricosuric Agents | Effect of probenecid, sulfinpyrazone and phenylbutazone inhibited

The following alterations of laboratory tests have been reported during salicylate therapy:

Laboratory Tests | Effect of Salicylates
Thyroid Function | Decreased PBI; increased T3 uptake
Urinary Sugar | False negative with glucose oxidase; false positive with Clinitest with high-dose salicylate therapy (2-5 g qd)
5 Hydroxyindole Acetic Acid | False negative with fluorometric test
Acetone, Ketone Bodies | False positive FeCl3 in Gerhardt reaction; red color persists with boiling
17-OH corticosteroids | False reduced values with >4.8 g qd salicylate
Vanilmandelic Acid | False reduced values
Uric Acid | May increase or decrease depending on dose
Prothrombin | Decreased levels; slightly increased prothrombin time

Pregnancy (Category C)

TERATOGENIC EFFECTS

Salicylic acid has been shown to be teratogenic in rats and monkeys. It is difficult to extrapolate from oral doses of acetylsalicylic acid used in these studies to topical administration as the oral dose to monkeys may represent 4 times the maximum daily human dose of salicylic acid when applied topically over a large body surface. There are no adequate and well-controlled studies in pregnant women. SALVAX should be used during pregnancy only if the potential benefit justifies the risk to the fetus.

Nursing Mothers

It is not known whether topically applied salicylic acid is excreted in human milk. Due to the fact that many drugs are excreted in human milk, caution should be exercised by physicians when administering SALVAX to nursing mothers and nursing mothers should certainly not apply SALVAX to the chest area or any other part of the body with which the nursing child's mouth is likely to come in contact.

Because of the potential for serious adverse reactions in nursing infants from the mother's use of SALVAX, a decision should be made whether to discontinue nursing or to discontinue the drug, taking into account the importance of the drug to the mother.

Carcinogenesis, Mutagenesis, Impairment of Fertility

No data are available concerning potential carcinogenic or reproductive effects of SALVAX. It has been shown to lack mutagenic potential in the Ames Salmonella test.

ADVERSE REACTIONS

Transient stinging, burning, itching or irritation is possible. Peeling of the skin may increase as the salicylic acid works to loosen excess keratin. If excessive burning, stinging or peeling occurs, discontinue use and consult your physician.

DOSAGE AND ADMINISTRATION

Clean and dry affected skin. Then apply SALVAX topically to cover affected skin twice per day, or as directed by a physician. Rub in until completely absorbed.

Follow these important directions to ensure proper foaming and maximum delivery of product:

- Shake canister vigorously before each use.
- Turn upside down (nozzle down) to dispense.
- Depress ridged portion of dispenser, as illustrated at right.

HOW SUPPLIED

SALVAX is supplied in a 70 gram or 2.5 ounce aerosolized canister bearing the NDC Number 23710-006-70, a 200 gram or 7.1 ounce aerosolized canister bearing the NDC Number 23710-006-02, and a 10 gram or 0.36 ounce aerosolized canister bearing the NDC Number 23710-006-01. The 10 gram canister is a physician-dispensed sample product.

STORAGE AND HANDLING

Store at room temperature 15° - 25°C (59° - 77°F).

Contains flammable materials. Contents under pressure. Do not puncture or incinerate. Do not expose to temperatures over 120°F (48°C) even when empty.

U.S. Patent 5,993,830.

Manufactured for Exeltis USA Dermatology, LLC. Florham Park, NJ 07932 / (877) 324-9349

Issue Date: July 2016

Exeltis
Rethinking healthcare

www.exeltisUSA.com

0062001-01

PRINCIPAL DISPLAY PANEL - 200 g Canister Label

NDC 23710-006-02

SALVAX®

salicylic acid 6%

HYDRATING TOPICAL FOAM

PRODERM TECHNOLOGY®

Rx only

NET WT. 7.1 OZ (200 g)

PRINCIPAL DISPLAY PANEL - 200 g Canister Carton

NDC 23710-006-02

SALVAX®

salicyclic acid
6%

HYDRATING TOPICAL FOAM
PRODERM TECHNOLOGY®

Exeltis
Rethinking healthcare

Rx only

NET WT. 7.1 OZ (200 g)